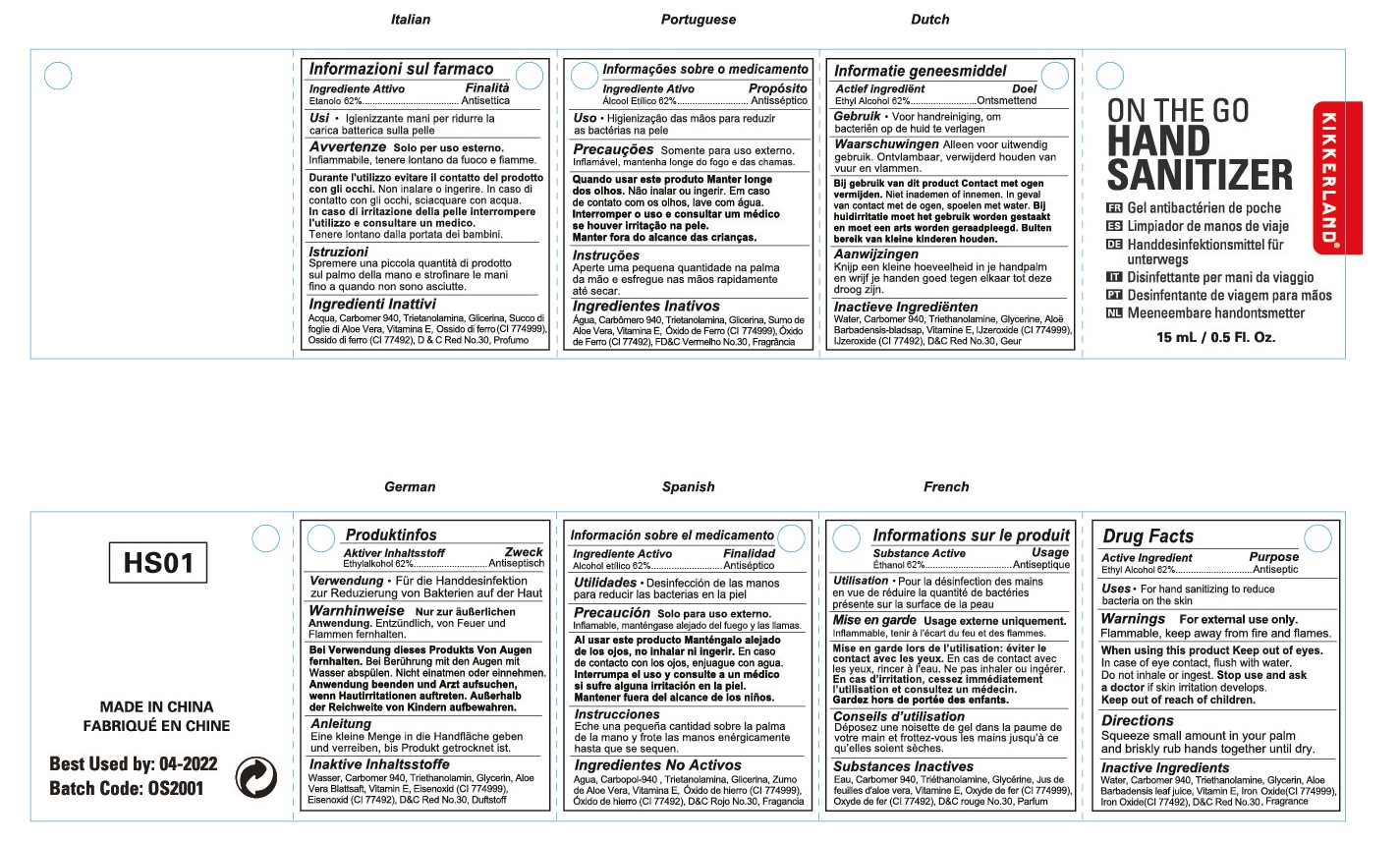 DRUG LABEL: HAND SANITIZER
NDC: 47993-282 | Form: GEL
Manufacturer: NINGBO JIANGBEI OCEAN STAR TRADING CO.,LTD
Category: otc | Type: HUMAN OTC DRUG LABEL
Date: 20201105

ACTIVE INGREDIENTS: ALCOHOL 62 g/112 mL
INACTIVE INGREDIENTS: CARBOMER 940; TRIETHANOLAMINE BENZOATE; ALOE VERA LEAF; WATER; GLYCERIN; TOCOPHEROL; FERROSOFERRIC OXIDE; FERRIC OXIDE YELLOW; D&C RED NO. 30

47993-282

Active ingredients

Ethyl Alcohol 62%

PURPOSE

Antiseptic

Uses：

For hand sanitizing to reduce bacteria on the skin.

Warnings:

For external use only.

Flammable. Keep away from fire or flame.

When using this product Keep out of reach of eyes. In case of eye contact, flush with water. Do not inhale or ingest.

Stop use and ask a doctor if skin irritation develops.

Keep out of reach of children.

Directions:

Squeeze small amount in your palm and briskly rub hands together until dry.

Inactive Ingredients:

Water,Carbomer 940,Triethanolamine,Glycerin,Aloe Barbadensis leaf juice,Vitamin E,Iron Oxide(CI 774999),Iron Oxide(CI 77492),D&C Red No.30,Fragrance